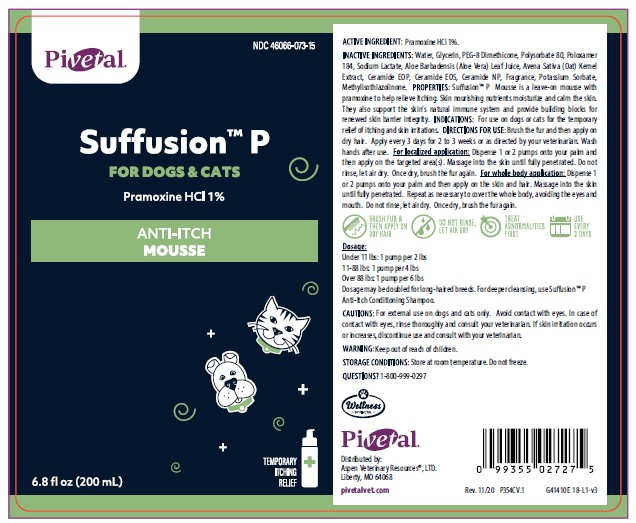 DRUG LABEL: Suffusion
NDC: 46066-073 | Form: LIQUID
Manufacturer: Aspen Veterinary Resource, LTD.
Category: animal | Type: OTC ANIMAL DRUG LABEL
Date: 20210423

ACTIVE INGREDIENTS: PRAMOXINE HYDROCHLORIDE 10 mg/1 mL
INACTIVE INGREDIENTS: WATER; GLYCERIN; PEG-8 DIMETHICONE; POLYSORBATE 80; POLOXAMER 184; ALOE VERA LEAF; AVENANTHRAMIDES; CERAMIDE 1; CERAMIDE EOS; CERAMIDE NP; POTASSIUM SORBATE; METHYLISOTHIAZOLINONE

DESCRIPTION

Suffusion™ P

FOR DOGS & CATS

ANTI-ITCH MOUSSE

ACTIVE INGREDIENTS: Pramoxine HCl 1%.

INACTIVE INGREDIENTS: Water, Glycerin, PEG-8 Dimethicone, Polysorbate 80, Poloxamer 184, Sodium Lactate, Aloe Barbadensis (Aloe) Leaf Juice, Avena Sativa (Oat) Kernel Extract, Ceramide EOP, Ceramide EOS, Ceramide NP, Fragrance, Potassium Sorbate, Methylisothiazolinone.

PROPERTIES: Suffusion™ P Mousse is a leave-on mousse with pramoxine to help relieve itching. Skin nourishing nutrients moisturize and calm the skin. The also support the skin's natural immune system and provide building blocks for renewed skin barrier integrity.

INDICATIONS AND USAGE

INDICATIONS: For use on dogs or cats for the temporary relief of itching and skin irritations.

DIRECTIONS FOR USE: Brush the fur and then apply on dry hair. Apply every 3 days for 2 to 3 weeks or as directed by your veterinarian. Wash hands after use.

For localized application: Dispense 1 or 2 pumps onto your palm and then apply on the targeted area(s). Massage into the skin until fully penetrated. Do not rinse, let air dry. Once dry, brush the fur again.

For whole body application: Dispense 1 or 2 pumps onto your palm and then apply on the skin and hair. Massage into the skin until fully penetrated. Repeat as necessary to cover the whole body, avoiding the eyes and mouth. Do not rinse, let air dry. Once dry, brush the fur again.

Dosage:

Under 11 lbs: 1 pump per 2 lbs

12-88 lbs: 1 pump per 4 lbs

Over 88 lbs: 1 pump per 6 lbs

Dosage may be doubled for long-haired dogs. For deeper cleansing, use Suffusion P Anti-Itch Conditioning Shampoo.

WARNINGS AND PRECAUTIONS

CAUTIONS: For external use on dogs and cats only. Avoid contact with eyes. In case of contact with eyes, rinse thoroughly and consult your veterinarian. If skin irritation occurs or increases, discontinue use and consult with your veterinarian.

WARNING: Keep out of reach of children.

STORAGE AND HANDLING

STORAGE CONDITIONS: Store at room temperature. Do not freeze.

QUESTIONS? 1-800-999-0297

Pivetal

Distributed by:
Aspen Veterinary Resources®, LTD.
Liberty, MO 64068

www.pivetalvet.com

PRINCIPAL DISPLAY PANEL - 6.8 OUNCE (200 mL) Bottle

Pivetal

NDC 46066-073-15

SUFFUSION™ P

FOR DOGS & CATS

Pramoxine HCl 1%

ANTI-ITCH MOUSSE

TEMPORARY ITCHING RELIEF

6.8 fl oz (200 mL)